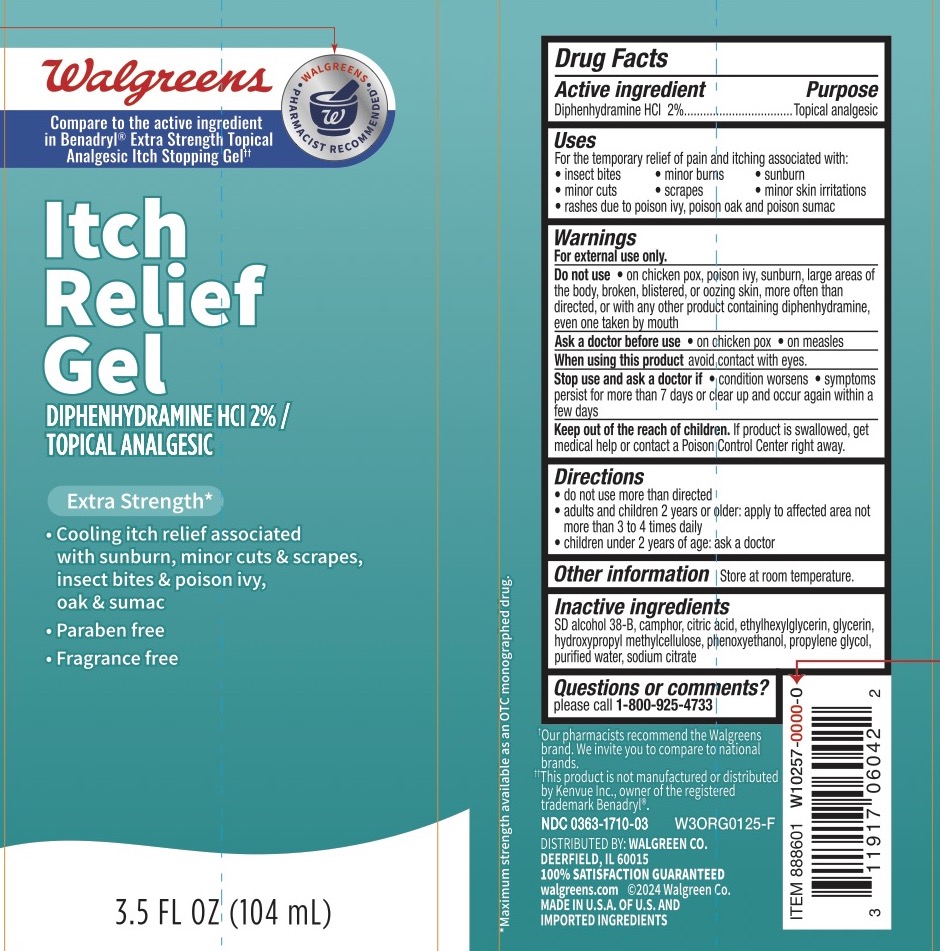 DRUG LABEL: Walgreens Stop Itch Gel
NDC: 0363-1710 | Form: GEL
Manufacturer: Walgreens Co
Category: otc | Type: HUMAN OTC DRUG LABEL
Date: 20250504

ACTIVE INGREDIENTS: DIPHENHYDRAMINE HYDROCHLORIDE 2 g/100 mL
INACTIVE INGREDIENTS: CAMPHOR (SYNTHETIC); HYPROMELLOSES; GLYCERIN; ALCOHOL; ETHYLHEXYLGLYCERIN; WATER; CITRIC ACID MONOHYDRATE; PHENOXYETHANOL; PROPYLENE GLYCOL; SODIUM CITRATE

Walgreens Stop Itch Gel, Diphenhydramine HCl 2%

ACTIVE INGREDIENT

Diphenhydramine HCl 2%

PURPOSE

Topical Analgesic.

INDICATIONS AND USAGE

For the temporary relief of pain and itching associated with insect bites, minor burns, sunburn, minor cuts, scrapes, minor skin irritations, and rashes due to poison ivy, oak, and sumac.

WARNINGS

For external use only. Do not use on large areas of the body, with any other products containing diphenhydramine, even one taken by mouth. Ask a doctor before use on chicken pox or measles. When using this product avoid contact with eyes. Stop use and ask a doctor if condition worsens, if symptoms persist for more than 7 days or clear up and occur again within a few days.

KEEP OUT OF REACH OF CHILDREN

If swallowed, get medical help or contact a Poison Control Center right away.

Do not use more than directed. Adults and children 12 years of age and older, apply to the affected area not more than 3 to 4 times daily. Children under 12 years of age: ask a doctor.

INACTIVE INGREDIENT

Camphor, Citric Acid, Ethylhexylglycerin, Glycerin, Hydroxypropyl Methylcellulose, Phenoxyethanol, Propylene Glycol, SD Alcohol 38-B, Sodium Citrate, Water.